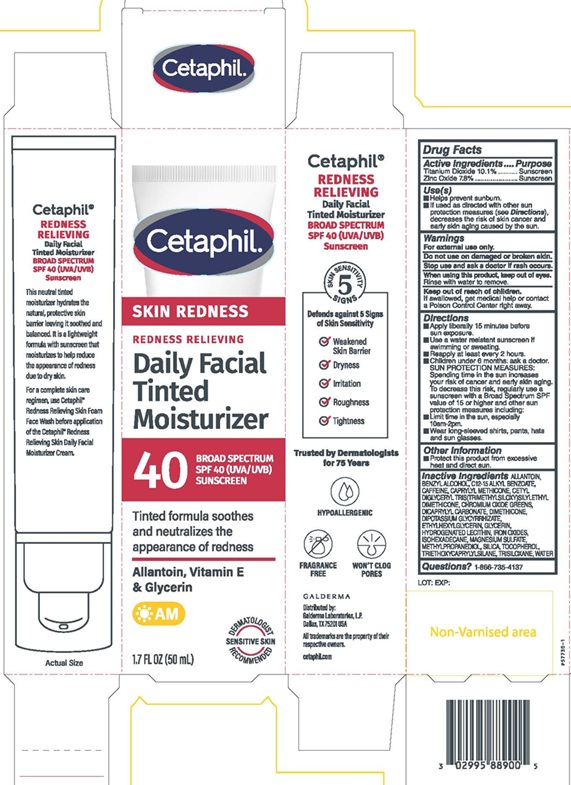 DRUG LABEL: Cetaphil Redness Relieving Daily Facial Moisturizer with sunscreen SPF 40
NDC: 0299-4138 | Form: CREAM
Manufacturer: Galderma Laboratories, L.P.
Category: otc | Type: HUMAN OTC DRUG LABEL
Date: 20251217

ACTIVE INGREDIENTS: TITANIUM DIOXIDE 101 mg/1 mL; ZINC OXIDE 78 mg/1 mL
INACTIVE INGREDIENTS: ALLANTOIN; BENZYL ALCOHOL; ALKYL (C12-15) BENZOATE; CAFFEINE; CAPRYLYL TRISILOXANE; CHROMIC OXIDE; DICAPRYLYL CARBONATE; DIMETHICONE; GLYCYRRHIZINATE DIPOTASSIUM; ETHYLHEXYLGLYCERIN; GLYCERIN; HYDROGENATED SOYBEAN LECITHIN; FERRIC OXIDE RED; ISOHEXADECANE; Magnesium Sulfate, Unspecified Form; METHYLPROPANEDIOL; SILICON DIOXIDE; TOCOPHEROL; TRIETHOXYCAPRYLYLSILANE; TRISILOXANE; WATER

Drug Facts

Active Ingredients

Titanium Dioxide 10.1%
Zinc Oxide 7.8 %

Purpose

Sunscreen

Use(s)

• Helps prevent sunburn
• If used as directed with other sun protection measures (see Directions) decreases the risk of skin cancer and early skin aging caused by the sun.

Warnings

For external use only
Do not use on damaged or broken skin.
Stop use and ask a doctor if rash occurs.
When using this product, keep out of eyes.
Rinse with water to remove.

Keep out of reach of children.

If swallowed, get medical help or contact a Poison Control Center right away.

Directions

• Apply liberally 15 minutes before sun exposure.
• Use a water resistant sunscreen if swimming or sweating
• Reapply at least every 2 hours.
• Children under 6 months: ask a doctor
SUN PROTECTION MEASURES: Spending time in the sun increases your risk of cancer and early skin aging. To decrease this risk, regularly use a sunscreen with a Broad Spectrum SPF value of 15 or higher and other sun protection measures including:
• Limit time in the sun, especially 10am – 2 pm.
• Wear long-sleeved shirts, pants, hats, and sun glasses.

Other Information

• Protect this product from excessive heat and direct sun.

Inactive Ingredients

ALLANTOIN, BENZYL ALCOHOL, C12-15 ALKYL BENZOATE, CAFFEINE, CAPRYLYL METHICONE, CETYL DIGLYCERYL TRIS(TRIMETHYLSILOXY) SILYLETHYL DIMETHICONE, CHROMIUM OXIDE GREENS, DICAPRYLYL CARBONATE, DIMETHICONE, DIPOTASSIUM GLYCYRRHIZATE, ETHYLHEXYLGLYCERIN, GLYCERIN, HYDROGENATED LECITHIN, IRON OXIDES, ISOHEXADECANE, MAGNESIUM SULFAGE, MEHYLPROPANEDIOL, SILICA, TOCOPHEROL, TRIETHOXYCAPRYLYLSILANE, TRISILOXANE, WATER

Questions?

1-866-735-4137

PRINCIPAL DISPLAY PANEL - 1.7 FL OZ (50 mL) carton

Cetaphil®

SKIN REDNESS
REDNESS RELIEVING
Daily Facial
Tinted
Moisturizer
40 BROAD SPECTRUM
SPF 40 (UVA/UVB)
SUNSCREEN

Tinted formula soothes
and neutralizes the
appearance of redness
Allantoin, Vitamin E
& Glycerin
AM
DERMATOLOGIST
SENSITIVE SKIN
RECOMMENDED
1.7 FL OZ (50 mL)

Distributed by:
Galderma Laboratories, L.P.
Dallas, TX 75201 USA
All trademarks are the property of their
respective owners.
cetaphil.com
P57730-1